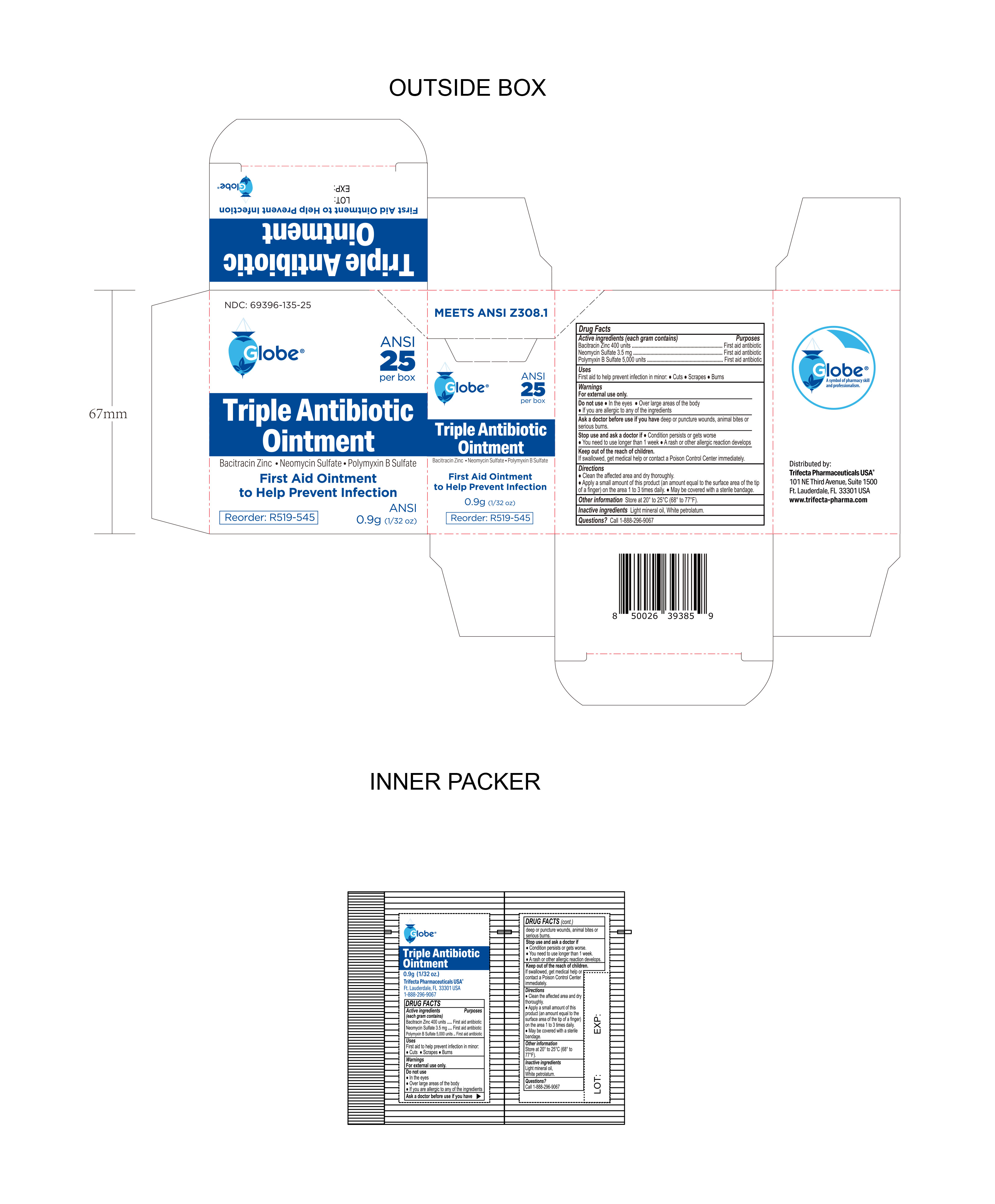 DRUG LABEL: Triple Antibiotic
NDC: 69396-135 | Form: OINTMENT
Manufacturer: Trifecta Pharmaceuticals USA LLC
Category: otc | Type: HUMAN OTC DRUG LABEL
Date: 20241231

ACTIVE INGREDIENTS: POLYMYXIN B SULFATE 5000 [USP'U]/1 g; NEOMYCIN SULFATE 3.5 mg/1 g; BACITRACIN ZINC 400 [USP'U]/1 g
INACTIVE INGREDIENTS: WHITE PETROLATUM; LIGHT MINERAL OIL

Globe Triple Antibiotic Ointment

Active Ingredient

Bacitracin Zinc 400 Units

Purpose

First Aid Antibiotic

Active ingredient

Neomycin Sulfate 3.5 mg

Purpose

First Aid Antibiotic

Active Ingredient

Polymyxin B Sulfate 5000 Units

Purpose

First Aid Antibiotic

Uses

First Aid to help prevent infection in minor:

- cuts
- scrapes
- burns

Warnings

For External Use Only.

Ask Doctor before use if you have

deep or puncture wounds

animal bites

serious burns

Do Not Use

- in eyes
- over large areas of the body
- if you are allergic to any of the ingredients

Stop Use and Ask Doctor if

- If conidition persists or gets worse
- You need to use longer than 1 week
- A rash or allergic reaction develops

Directions

- Clean the affected area and dry thoroughly
- Apply a small amount of the product (an amount equal to the surface area of the tip of a finger) on the area 1 to 3 times daily
- May be covered with a sterile bandage

Inactive Ingredients

light mineral oil and white petrolatum

Questions

Call 1-888-296-9067

Storage Information

Store at 20° to 25°C (68° to 77°F).

Keep out of reach of children

If swallowed, get medical help or contact a Poison Control Center immediately.

Other Information

Distributed By:

Trifecta Pharmaceuticals USA®

101 NE Third Avenue, Suite 1500

Ft. Lauderdale, FL. 33301 USA

www.trifecta-pharma.com

Reorder: R519-545